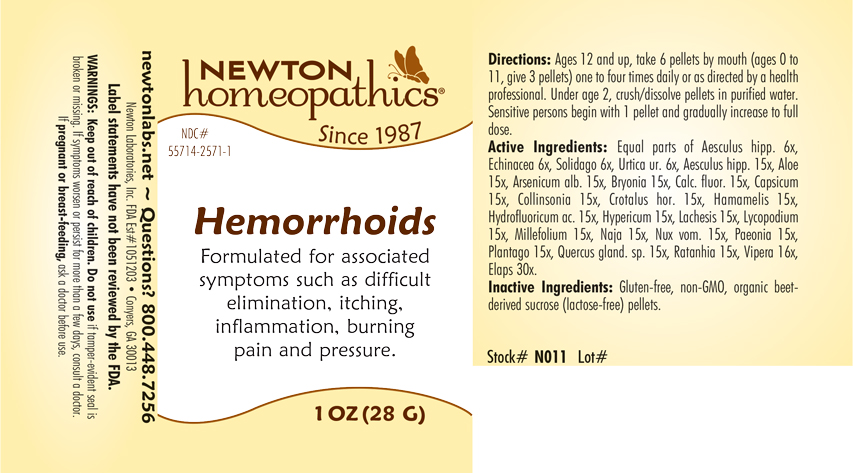 DRUG LABEL: Hemorrhoids
NDC: 55714-2571 | Form: PELLET
Manufacturer: Newton Laboratories, Inc.
Category: homeopathic | Type: HUMAN OTC DRUG LABEL
Date: 20210315

ACTIVE INGREDIENTS: HYPERICUM PERFORATUM 15 [hp_X]/1 g; LACHESIS MUTA VENOM 15 [hp_X]/1 g; LYCOPODIUM CLAVATUM SPORE 15 [hp_X]/1 g; ACHILLEA MILLEFOLIUM 15 [hp_X]/1 g; NAJA NAJA VENOM 15 [hp_X]/1 g; STRYCHNOS NUX-VOMICA SEED 15 [hp_X]/1 g; PAEONIA OFFICINALIS ROOT 15 [hp_X]/1 g; PLANTAGO MAJOR 15 [hp_X]/1 g; QUERCUS ROBUR NUT 15 [hp_X]/1 g; KRAMERIA LAPPACEA ROOT 15 [hp_X]/1 g; VIPERA BERUS VENOM 16 [hp_X]/1 g; ECHINACEA, UNSPECIFIED 6 [hp_X]/1 g; SOLIDAGO VIRGAUREA FLOWERING TOP 6 [hp_X]/1 g; URTICA URENS 6 [hp_X]/1 g; ARSENIC TRIOXIDE 15 [hp_X]/1 g; MICRURUS CORALLINUS VENOM 30 [hp_X]/1 g; HORSE CHESTNUT 15 [hp_X]/1 g; ALOE 15 [hp_X]/1 g; BRYONIA ALBA ROOT 15 [hp_X]/1 g; CALCIUM FLUORIDE 15 [hp_X]/1 g; CAPSICUM 15 [hp_X]/1 g; COLLINSONIA CANADENSIS ROOT 15 [hp_X]/1 g; CROTALUS HORRIDUS HORRIDUS VENOM 15 [hp_X]/1 g; HAMAMELIS VIRGINIANA ROOT BARK/STEM BARK 15 [hp_X]/1 g; HYDROFLUORIC ACID 15 [hp_X]/1 g
INACTIVE INGREDIENTS: SUCROSE

Hemorrhoids 2571P

INDICATIONS & USAGE SECTION

Formulated for associated symptoms such as difficult elimination, itching, inflammation, burning pain and pressure.

DOSAGE & ADMINISTRATION SECTION

Directions: Ages 12 and up, take 6 pellets by mouth (ages 0 to 11, give 3 pellets) one to four times daily or as directed by a health professional. Under age 2, crush/dissolve pellets in purified water. Sensitive persons begin with 1 pellet and gradually increase to full dose.

OTC - ACTIVE INGREDIENT SECTION

Equal parts of Aesculus hippocastanum 6x, Echinacea 6x, Solidago virgaurea 6x, Urtica urens 6x, Aesculus hippocastanum 15x, Aloe 15x, Arsenicum album 15x, Bryonia 15x, Calcarea fluorica 15x, Capsicum annuum 15x, Collinsonia canadensis 15x, Crotalus horridus 15x, Hamamelis virginiana 15x, Hydrofluoricum acidum 15x, Hypericum perforatum 15x, Lachesis mutus 15x, Lycopodium clavatum 15x, Millefolium 15x, Naja tripudians 15x, Nux vomica 15x, Paeonia officinalis 15x, Plantago major 15x, Quercus glandium spiritus 15x, Ratanhia 15x, Vipera berus 16x, Elaps corallinus 30x.

OTC - PURPOSE SECTION

Formulated for associated symptoms such as difficult elimination, itching, inflammation, burning pain and pressure.

INACTIVE INGREDIENT SECTION

Inactive Ingredients: Gluten-free, non-GMO, organic beet-derived sucrose (lactose-free) pellets.

QUESTIONS SECTION

newtonlabs.net - Questions? 800.448.7256

Newton Laboratories, Inc. FDA Est # 1051203 - Conyers, GA 30013

WARNINGS SECTION

WARNINGS: Keep out of reach of children. Do not use if tamper-evident seal is broken or missing. If symptoms worsen or persist for more than a few days, consult a doctor. If pregnant or breast-feeding, ask a doctor before use.

OTC - PREGNANCY OR BREAST FEEDING SECTION

If pregnant or breast-feeding, ask a doctor before use.

OTC - KEEP OUT OF REACH OF CHILDREN SECTION

Keep out of reach of children